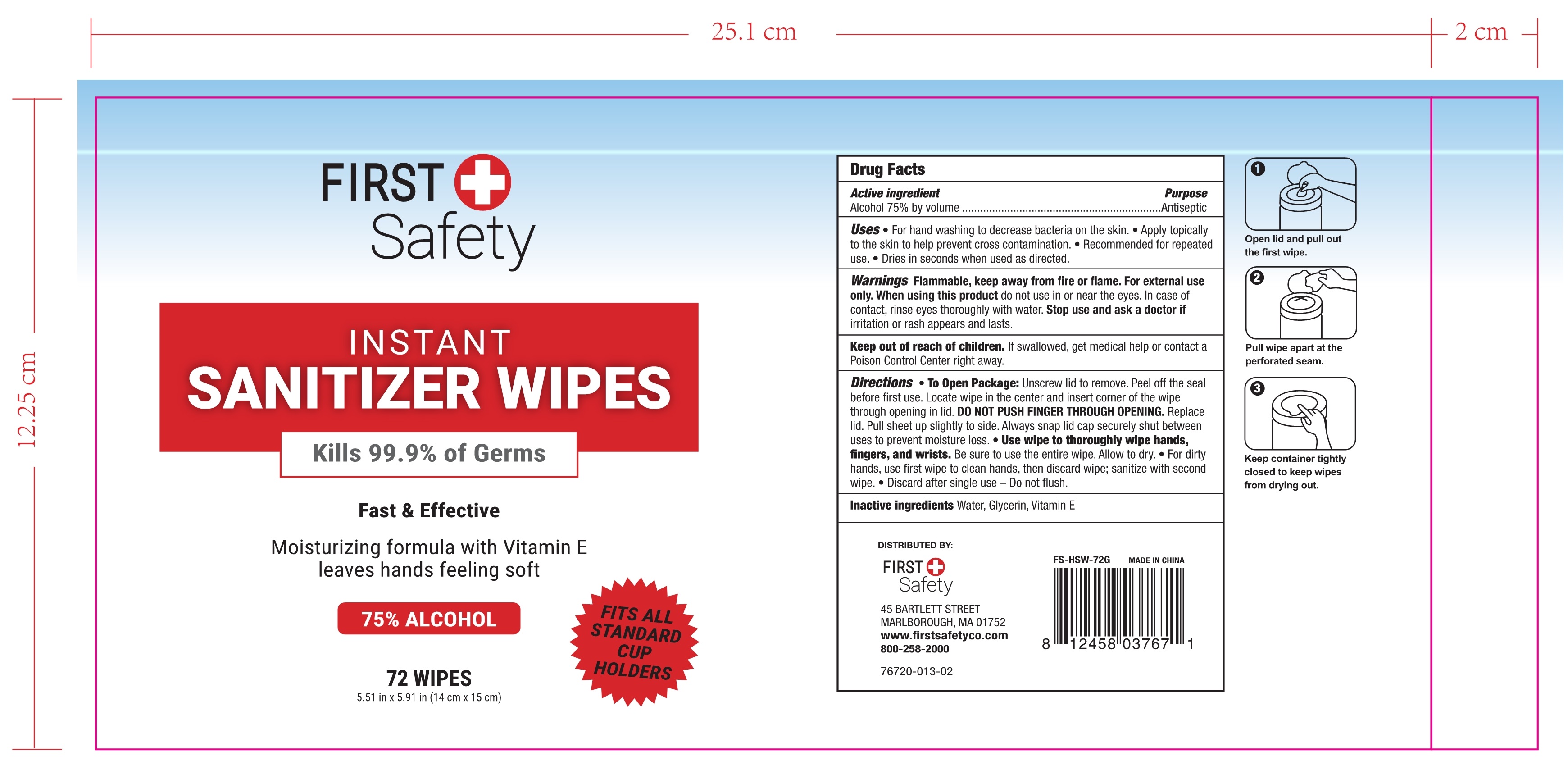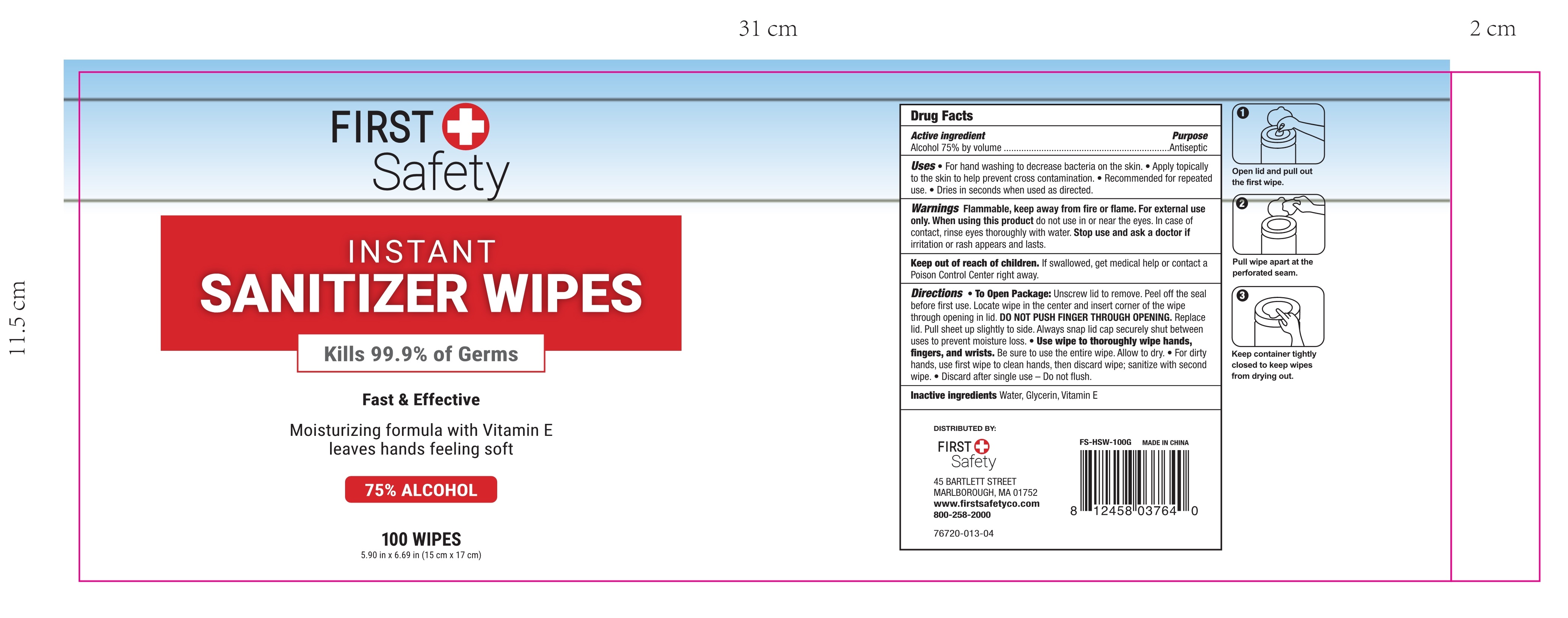 DRUG LABEL: SANITIZER WIPES
NDC: 74763-013 | Form: CLOTH
Manufacturer: ZHEJIANG GAFLE AUTO CHEMICAL CO.,LTD
Category: otc | Type: HUMAN OTC DRUG LABEL
Date: 20220328

ACTIVE INGREDIENTS: ALCOHOL 75 mL/100 1
INACTIVE INGREDIENTS: WATER; GLYCERIN; .ALPHA.-TOCOPHEROL

74763-013 SANITIZER WIPES

ACTIVE INGERDIENT

Alcohol 75% by volume

PURPOSE

Antiseptic

USES

For hand washing to decrease bacteria on the skin.
Apply topically to the skin to help prevent cross contamination.
Recommended for repeated use.
Dries in seconds when used as directed.

WARNINGS

Flammable, keep away from fire or flame. For external use only.

When using this product do not use in or near the eyes. In case of contact, rinse eyes thoroughly with water.

Stop use and ask a doctor if irritation or rash appears and lasts.

Keep out of reach of children. If swallowed, get medical help or contact a Poison Control Center right away.

When using this product do not use in or near the eyes. In case of contact, rinse eyes thoroughly with water.

When using this product do not use in or near the eyes. In case of contact, rinse eyes thoroughly with water.

Stop use and ask a doctor if irritation or rash appears and lasts.

Keep out of reach of children. If swallowed, get medical help or contact a Poison Control Center right away.

Stop use and ask a doctor if irritation or rash appears and lasts.

Keep out of reach of children. If swallowed, get medical help or contact a Poison Control Center right away.

DIRECTIONS

To Open Package: Unscrew lid to remove. Peel off the seal before first use. Locate wipe in the center and insert corner of the wipe through opening in lid. DO NOT PUSH FINGER THROUGH OPENING. Replace lid. Pull sheet up slightly to side. Always snap lid cap securely shut between uses to prevent moisture loss. Use wipe to thoroughly wipe hands, fingers, and wrists. Be sure to use the entire wipe. Allow to dry. For dirty hands, use first wipe to clean hands, then discard wipe; sanitize with second wipe. Discard after single use - Do not flush.

OTHER INFORMATION

/

INACTIVE INGERDIENTS

Water, Glycerin, Vitamin E